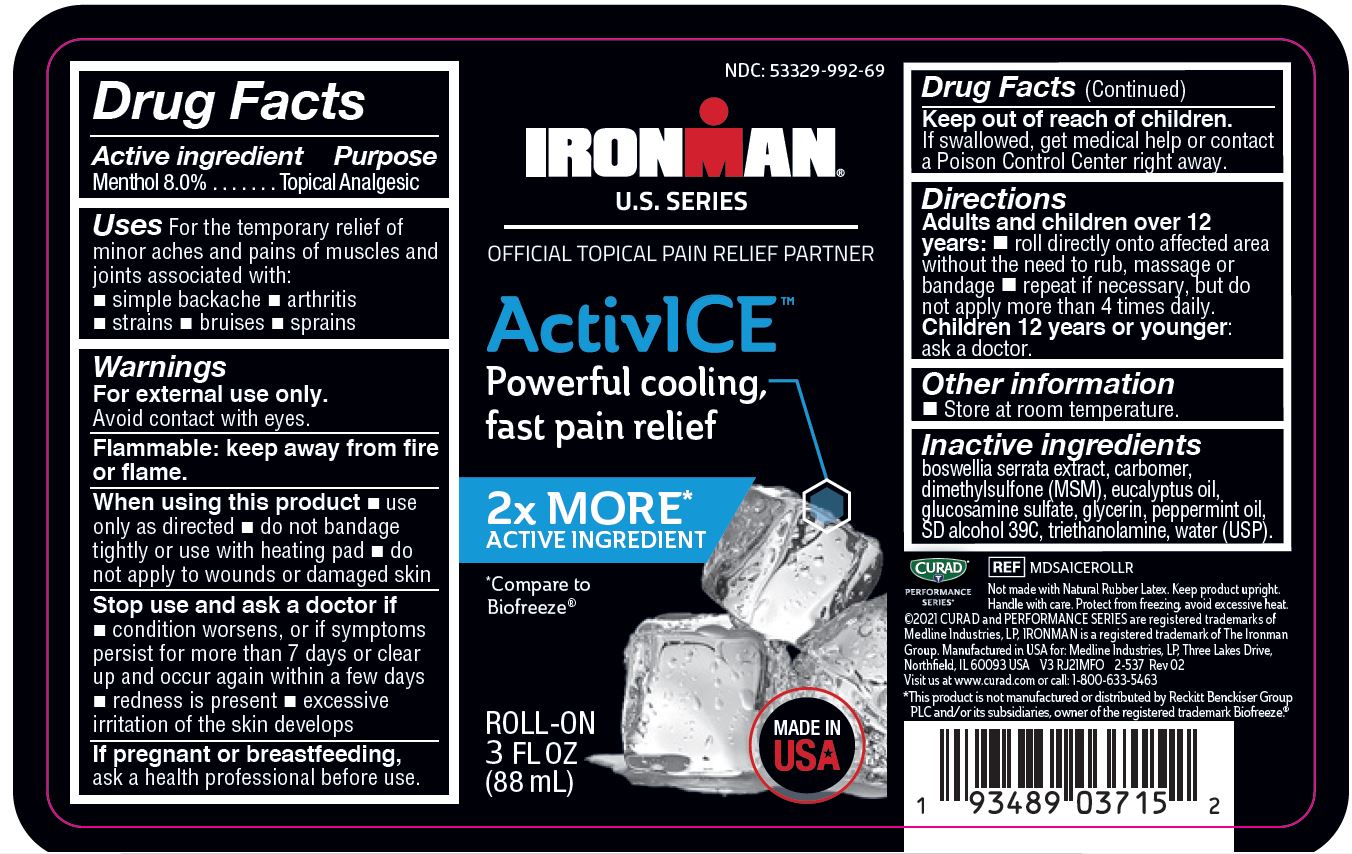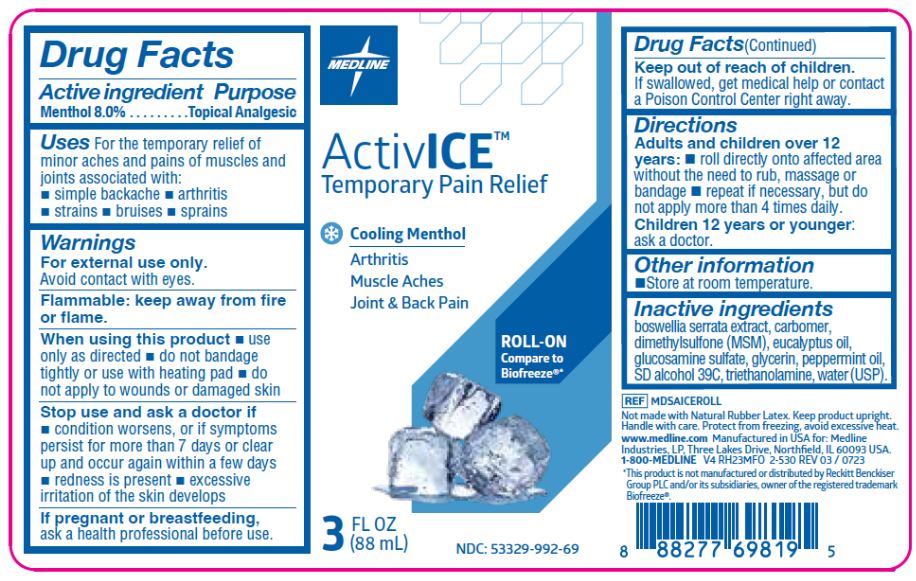 DRUG LABEL: ActivICE
NDC: 53329-992 | Form: LIQUID
Manufacturer: Medline Industries, LP
Category: otc | Type: HUMAN OTC DRUG LABEL
Date: 20241212

ACTIVE INGREDIENTS: MENTHOL 80 g/1000 g
INACTIVE INGREDIENTS: CARBOMER 940; ALCOHOL; GLUCOSAMINE SULFATE; TROLAMINE; GLYCERIN; BOSWELLIA SERRATA RESIN OIL; DIMETHYL SULFONE; PEPPERMINT OIL; WATER; EUCALYPTUS OIL

992 ActivICE roll-on

Active Ingredient

Menthol 8.0%

Purpose

Topical Analgesic

Uses

For the temporary relief of
minor aches and pains of muscles and
joints associated with:

- simple backache
- arthritis
- strains
- bruises
- sprains

Warnings

For external use only.
Avoid contact with eyes.
Flammable: keep away from fire
or flame.

When using this product

- use only as directed
- do not bandage tightly or use with heating pad
- do not apply to wounds or damaged skin

Stop use and ask doctor if

- condition worsens, or if symptoms
- persist for more than 7 days or clear
- up and occur again within a few days
- redness is present
- excessiveirritation of the skin develops

If pregnant or breastfeeding,

ask a health professional before use.

Keep out of reach of children.

If swallowed, get medical help or contact
a Poison Control Center right away.

Directions

Adults and children over 12
years:

roll directly onto affected area without the need to rub, massage or bandage

repeat if necessary, but do not apply more than 4 times daily.

Children 12 years or younger:
ask a doctor.

Other information

- Store at room temperature.

Inactive Ingredients

boswellia serrata extract, carbomer,
dimethylsulfone(MSM), eucalyptus oil,
glucosamine sulfate, glycerin,
peppermint oil, SD alcohol 39C,
triethanolamine, water.

Manufacturing Information

Manufactured for:
Medline Industries, LP
Three Lakes Drive, Northfield, IL 60093 USA
Made in USA
www.medline.com
1-800-MEDLINE (633-5463)
REF: MDSAICEROLL, V4 RH23MFO

REF: MDSAICEROLLR, V3 RJ21MFO